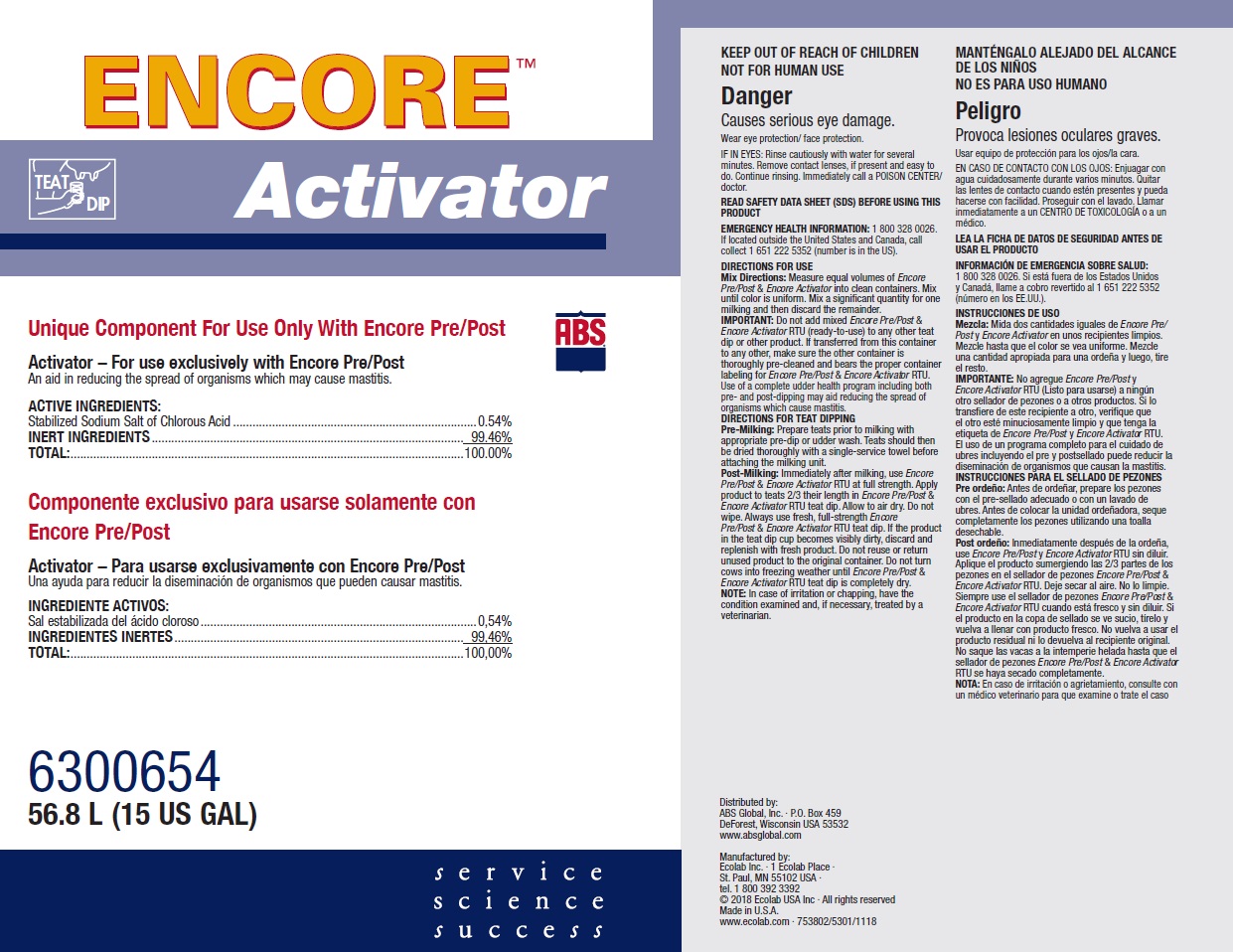 DRUG LABEL: Encore Activator
NDC: 59282-108 | Form: SOLUTION
Manufacturer: ABS Global Inc.
Category: animal | Type: OTC ANIMAL DRUG LABEL
Date: 20211028

ACTIVE INGREDIENTS: CHLOROUS ACID 5.4 mg/1 mL
INACTIVE INGREDIENTS: WATER

KEEP OUT OF REACH OF CHILDREN

NOT FOR HUMAN USE

Danger

Causes serious eye damage.

Wear eye protection/ face protection.

VETERINARY INDICATIONS

DIRECTIONS FOR USE

Mix Directions: Measure equal volumes of Encore Pre/Post & Encore Activator into clean containers. Mix until color is uniform. Mix a significant quantity for one milking and then discard the remainder.

IMPORTANT: Do not add mixed Encore Pre/Post & Encore Activator RTU (ready-to-use) to any other teat dip or other product. If transferred from this container to any other, make sure the other container is thoroughly pre-cleaned and bears the proper container labeling for Encore Pre/Post & Encore Activator RTU. Use of a complete udder health program including both pre- and post-dipping may aid reducing the spread of organisms which cause mastitis.

DIRECTIONS FOR TEAT DIPPING

Pre-Milking: Prepare teats prior to milking with appropriate pre-dip or udder wash. Teats should then be dried thoroughly with a single-service towel before attaching the milking unit.

Post-Milking: Immediately after milking, use Encore Pre/Post & Encore Activator RTU at full strength. Apply product to teats 2/3 their length in Encore Pre/Post & Encore Activator RTU teat dip. Allow to air dry. Do not wipe. Always use fresh, full-strength Encore

Pre/Post & Encore Activator RTU teat dip. If the product in the teat dip cup becomes visibly dirty, discard and replenish with fresh product. Do not reuse or return unused product to the original container. Do not turn cows into freezing weather until Encore Pre/Post & Encore Activator RTU teat dip is completely dry.

NOTE: In case of irritation or chapping, have the condition examined and, if necessary, treated by a veterinarian.

OTHER SAFETY INFORMATION

IF IN EYES: Rinse cautiously with water for several minutes. Remove contact lenses, if present and easy to do. Continue rinsing. Immediately call a POISON CENTER/doctor.

READ SAFETY DATA SHEET (SDS) BEFORE USING THIS PRODUCT

EMERGENCY HEALTH INFORMATION: 1 800 328 0026. If located outside the United States and Canada, call collect 1 651 222 5352 (number is in the US).

Principal display panel and representative label

ENCORE

Activator

Unique Component For Use Only With Encore Pre/Post

Activator – For use exclusively with Encore Pre/Post

An aid in reducing the spread of organisms which may cause mastitis.

ACTIVE INGREDIENTS:

Stabilized Sodium Salt of Chlorous Acid...............0.54%

INERT INGREDIENTS....................................99.46%

TOTAL:..........................................................100.00%

630065456.8 L (15 US GAL)

Distributed by:

ABS Global, Inc. ∙ P.O. Box 459

DeForest, Wisconsin USA 53532

www.absglobal.com

Manufactured by:

Ecolab Inc. ∙ 1 Ecolab Place ∙

St. Paul, MN 55102 USA ∙

tel. 1 800 392 3392

© 2018 Ecolab USA Inc ∙ All rights reserved

Made in U.S.A.

www.ecolab.com ∙ 753802/5301/1118